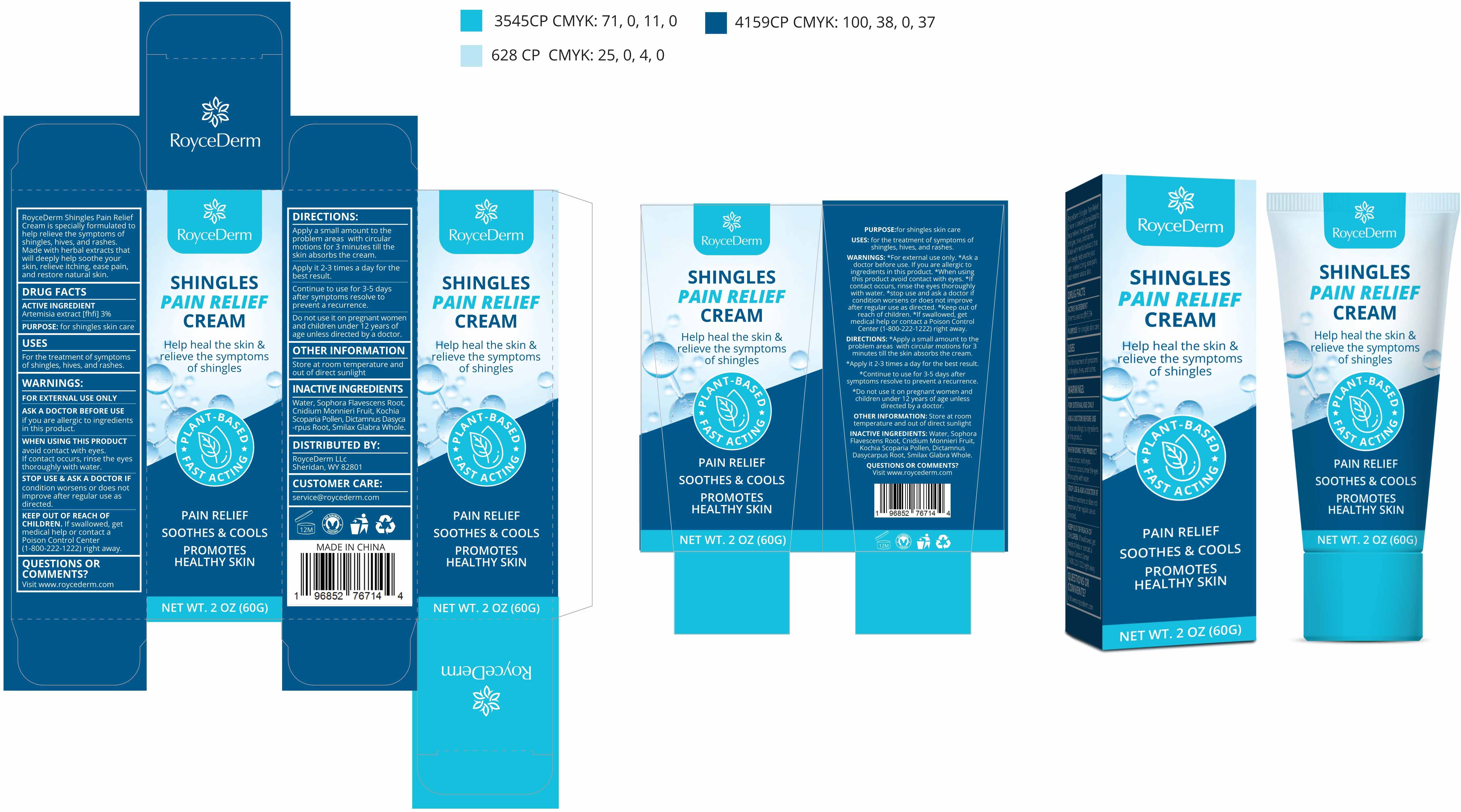 DRUG LABEL: Shingles Pain Relief Cream
NDC: 81799-009 | Form: CREAM
Manufacturer: Ehy Holdings LLC
Category: otc | Type: HUMAN OTC DRUG LABEL
Date: 20230224

ACTIVE INGREDIENTS: WORMWOOD 3 g/100 g
INACTIVE INGREDIENTS: DICTAMNUS DASYCARPUS ROOT; WATER; SOPHORA FLAVESCENS ROOT; SMILAX GLABRA WHOLE; CNIDIUM MONNIERI FRUIT; BASSIA SCOPARIA POLLEN

81799-009
Shingles Pain Relief Cream

Active Ingredient(s)

Artemisia extract [fhfi] 3%

Purpose

for shingles skin care

Use

For the treatment of symptomsof shingles, hives, and rashes.

Warnings

FOR EXTERNAL USE ONLY

Do not use

it on pregnant womenand children under 12 years ofage unless directed by a doctor

WHEN USING

avoid contact with eyeslf contact occurs, rinse the eyesthoroughly with water.

STOP USE

condition worsens or does notimprove after regular use asdirected

KEEP OUT OF REACH OF CHILDREN

If swallowed, getmedical help or contact aPoison Control Center(1-800-222-1222) right away.

Directions

Apply a small amount to theproblem areas with circularmotions for 3 minutes till theskin absorbs the cream.
Apply it 2-3 times a day for thebest result.

Other information

Store at room temperature andout of direct sunlight

Inactive ingredients

Water, Sophora Flavescens Root,Cnidium Monnieri Fruit, KochiaScoparia Pollen, Dictamnus Dasyca-rpus Root, Smilax Glabra Whole

ASK DOCTOR

if you are allergic to ingredientsin this product.

QUESTIONS

Visit www.roycederm.com

Package Label - Principal Display Panel

81799-009-01